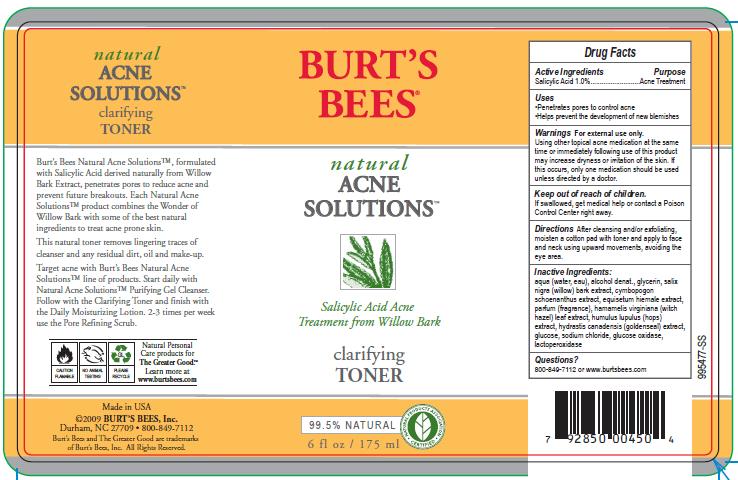 DRUG LABEL: Natural Acne Solutions Clarifying Toner
NDC: 26052-017 | Form: LIQUID
Manufacturer: Burt's Bees, Inc.
Category: otc | Type: HUMAN OTC DRUG LABEL
Date: 20100816

ACTIVE INGREDIENTS: SALICYLIC ACID 1.0 mL/100 mL

Drug Facts

Active Ingredients

Salicylic Acid 1.0%

Purpose

Acne Treatment

Uses

- Penetrates pores to control acne
- Helps prevent the development of new blemishes

Warnings

For external use only.

Using other topical acne medication at the same time or immediately following use of this product may increase dryness or irritation of the skin. If this occurs, only one medication should be used unless directed by a doctor.

Keep out of reach of children

f swallowed, get medical help or contact a Poison Control Center right away.

Directions

After cleansing and/or exfoliating, moisten a cotton pad with toner and apply to face and neck using upward movements, avoiding the eye area.

Inactive Ingredients

aqua (water, eau), alcohol denat., glycerin, salix nigra (willow) bark extract, cymbopogon schoenanthus extract, equisetum hiemale extract, parfum (fragrance), hamamelis virginiana (witch hazel) leaf extract, humulus lupulus (hops) extract, hydrastis canadensis (goldenseal) extract, glucose, sodium chloride, glucose oxidase, lactoperoxidase

QUESTIONS

800-849-7112 or www.burtsbees.com

PDP Package Label

bottle